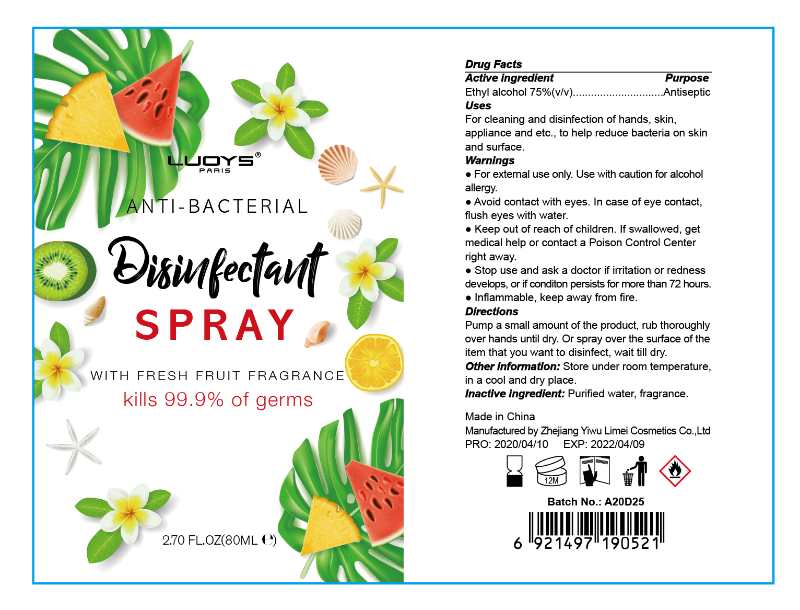 DRUG LABEL: LUOYS Antibacterial Disinfectant
NDC: 74765-002 | Form: SPRAY
Manufacturer: ZheJiang Yiwu Limei Cosmetics Co., Ltd
Category: otc | Type: HUMAN OTC DRUG LABEL
Date: 20200416

ACTIVE INGREDIENTS: ALCOHOL 75 mL/100 mL
INACTIVE INGREDIENTS: WATER

NA

Active Ingredient(s)

Ethyl Alcohol 75% v/v. Purpose: Antiseptic

Purpose

Antiseptic

Use

For cleaning and disinfection of hands, skin, appliance and etc., to help decrease bacteria on skin and surface

Warnings

For external use only. Use with caution for alcohol allergy

Aviod contact with eyes. In case of eye contact, flush eyes with water

Flammable. Keep away from heat or flame

Stop use and ask a doctor if irritation or redness develops, or if condition persists for more than 72 hours

Keep out of reach of children. If swallowed, get medical help or contact a Poison Control Center right away.

Directions

- Pump a small amount of the product
- Rub thoroughly over hands untill dry
- Or spray over the surface of the item that you want to disinfect, wait until dry

Other information

- Store under room temperature in a cool and dry place

Inactive ingredients

Water, fragrance